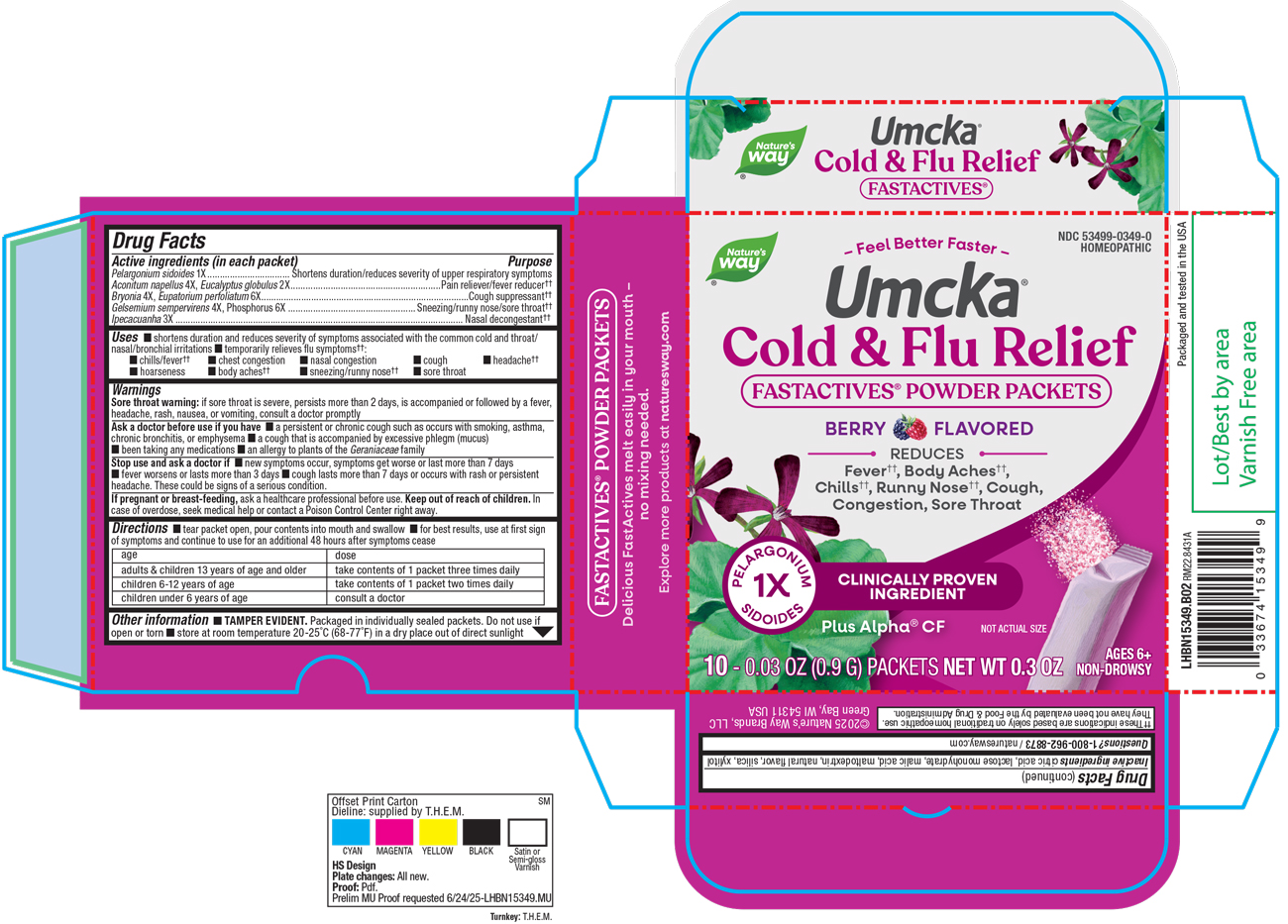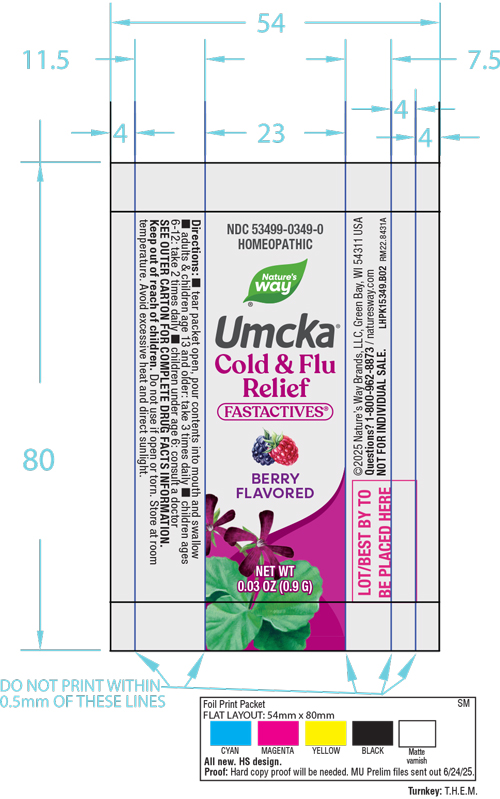 DRUG LABEL: Cold Flu Relief Berry
NDC: 53499-0349 | Form: POWDER
Manufacturer: Schwabe North America, Inc
Category: homeopathic | Type: HUMAN OTC DRUG LABEL
Date: 20250731

ACTIVE INGREDIENTS: PELARGONIUM SIDOIDES ROOT 1 [hp_X]/912 mg; ACONITUM NAPELLUS 4 [hp_X]/912 mg; EUCALYPTUS GLOBULUS LEAF 2 [hp_X]/912 mg; BRYONIA ALBA ROOT 4 [hp_X]/912 mg; EUPATORIUM PERFOLIATUM FLOWERING TOP 6 [hp_X]/912 mg; GELSEMIUM SEMPERVIRENS ROOT 4 [hp_X]/912 mg; PHOSPHORUS 6 [hp_X]/912 mg; IPECAC 3 [hp_X]/912 mg
INACTIVE INGREDIENTS: CITRIC ACID MONOHYDRATE; LACTOSE MONOHYDRATE; MALIC ACID; MALTODEXTRIN; SILICON DIOXIDE; XYLITOL

Cold Flu Relief FastActives Berry Packets

Active Ingredients

Pelargonium sidoides 1X

Aconium napellus 4X

Eucalyptus globulus 2X

Bryonia 4X

Eupatorium perfoliatum 6X

Gelsemium sempervirens 4X

Phosphorus 6X

Ipecacuanha 3X

Inactive Ingredients

Citric Acid

Lactose Monohydrate

Malic Acid

Maltodextrin

Natural Flavor

Silica

Xylitol

Dosage & Administration

Directions

Tear packet open, pour contents into mouth and swallow.

For best results, use at first sign of symptoms and continue to use for an additional 48 hours after symptoms cease.

Adults & children 13 years of age and older: take contents of 1 packet three times daily.

Children 6-12 years of age: take contents of 1 packet two times daily.

Children under 6 years of age: consult a doctor.

Indications & Usage

Shortens duration and reduces severity of symptoms associated with the common cold and throat/nasal/bronchial irritations, and temporarily relieves flu symptoms: chills/fever, chest congestion, nasal congestion, cough, headache, hoarseness, body aches, sneezing/runny nose, sore throat.

Purpose

Shortens duration and reduces severity of symptoms associated with the common cold and throat/nasal/bronchial irritations, and temporarily relieves flu symptoms: chills/fever, chest congestion, nasal congestion, cough, headache, hoarseness, body aches, sneezing/runny nose, sore throat.

Warnings

Sore throat warning: if sore throat is severe, persists more than 2 days, is accompanied or following by a fever, headache, rash, nausea, or vomiting, consult a doctor promptly.

Ask Doctor

Ask a doctor before use if you have a persistent or chronic cough such as occurs with smoking, asthma, chronic bronchitis, or emphysemsa, a cough that is accompanied by excessive phlegm (mucus), been taking any medications, an allergy to plants of the Geraniaceae family.

Stop Use

Stop use and ask a doctor if new symptoms occur, symptoms get worse or last more than 7 days, fever worsens or lasts more than 3 days, cough lasts more than 7 days or occurs with rash or persistent headache.

These could be signs of a serious condition.

Pregnancy or breast feeding

If pregnant or breast-feeding, ask a healthcare professional before use.

Keep out of reach of children

Overdose

In case of overdose, seek medical help or contact a Posion Control Center right away.